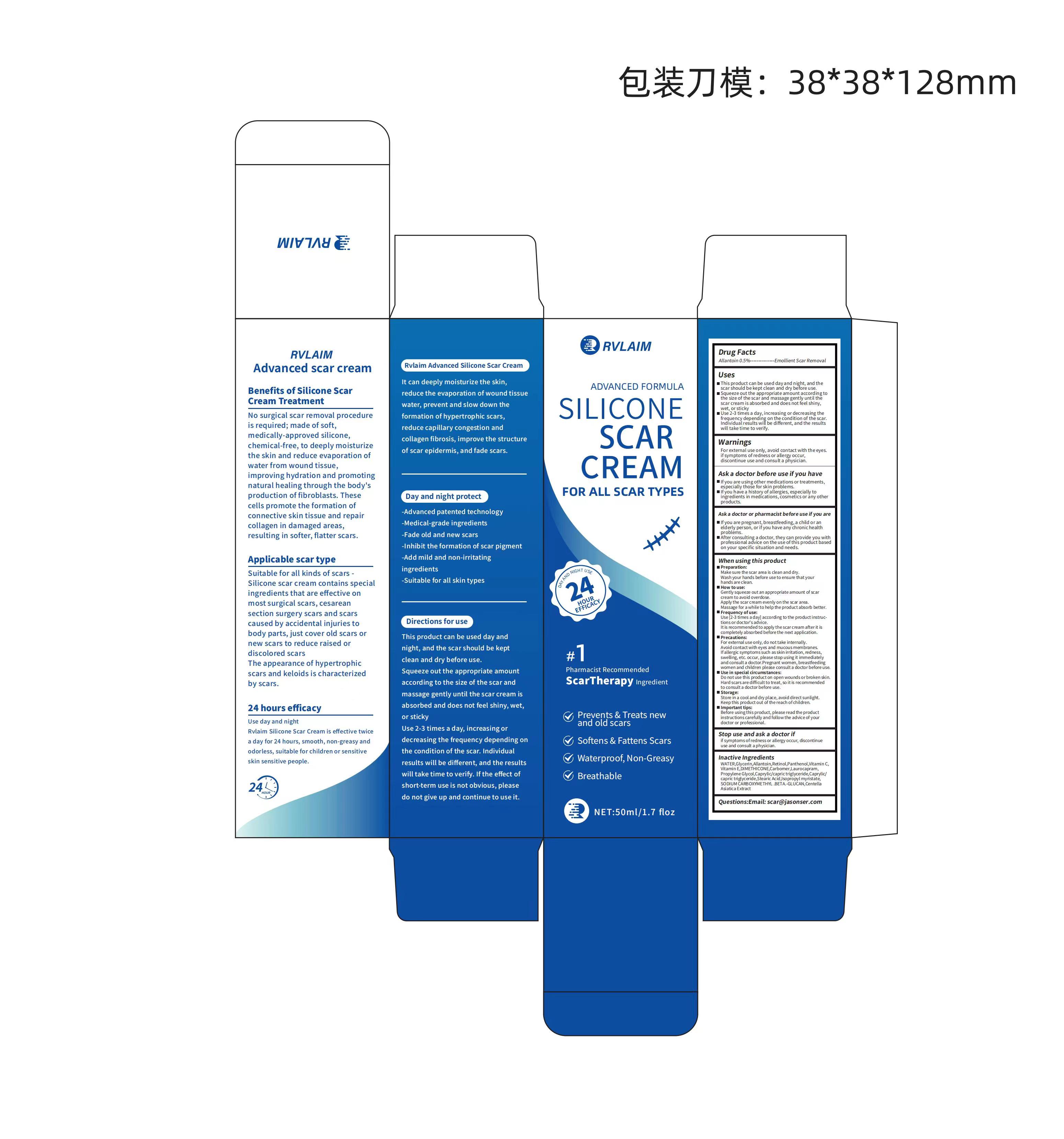 DRUG LABEL: RVLAIM SILICONE SCAR Cream
NDC: 84433-001 | Form: CREAM
Manufacturer: Shenzhen Jiucai Ecommerce Co., Ltd
Category: otc | Type: HUMAN OTC DRUG LABEL
Date: 20240619

ACTIVE INGREDIENTS: ALLANTOIN 5 g/100 mL
INACTIVE INGREDIENTS: DIMETHICONE; ALPHA-TOCOPHEROL; STEARIC ACID; ASCORBIC ACID; CARBOMER HOMOPOLYMER, UNSPECIFIED TYPE; MEDIUM-CHAIN TRIGLYCERIDES; LAUROCAPRAM; ISOPROPYL MYRISTATE; GLYCERIN; PANTHENOL; PROPYLENE GLYCOL; SODIUM CARBOXYMETHYL .BETA.-GLUCAN (DS 0.65-0.85); CENTELLA ASIATICA TRITERPENOIDS; RETINOL; WATER

RVLAIM SILICONE SCAR CREAM

RVLAIM SILICONE SCAR CREAM

ACTIVE INGREDIENT

Allantoin 0.5%

PURPOSE

Emollient Scar Removal

INDICATIONS AND USAGE

This product can be used day and night, and thescar should be kept clean and dry before use.
Squeeze out the appropriate amount according tothe size of the scar and massage gently until thescar cream is absorbed and does not feel shiny,wet, or sticky.
Use 2-3 times a day,increasing or decreasing thefrequency depending on the condition of the scar.Individualresults will be different, and the resultswill take time to verify.

WARNINGS

For external use only, avoid contact with the eyesif symptoms of redness or allergy occur,discontinue use and consuit a physician.

DO NOT USE

if you are using other medications or treatmentsespecially those for skin problems.
lf you have a history of allergies, especially toingredients in medications, cosmetics or any otherproducts.
If you are pregnant, breastfeeding, a child or anelderly person, or if you have any chronic health problems.
After consulting a doctor, they can provide you withprofessional advice on the use of this product basedon your specific situation and needs.

WHEN USING

Preparation:
Make sure the scar area is clean and dry.Wash your hands before use to ensure thatyourhands are clean.
How to use:
Gently squeeze out an appropriate amount of scarcream to avoid overdose.Applythe scar cream evenlyon the scar area.Massage for a while to help the product absorb better.
Frequency ofuse:
Use [2-3 times a day] according to the productinstructions or doctor's advice.Itis recommended to apply the scar cream after it iscompletely absorbed before the next application.
Precautions:
For external use only, do not take internally.Avoid contact with eyes and mucous membranes.Ifallergic symptoms such as skin irritation,redness.swelling,etc.occur,please stop using it immediatelyand consult a doctor.Pregnant women,breastfeedingwomen and children please consult a doctor before use.
Use in special circumstances:
Do not use this product on open wounds or broken skin.Hard scars are difficult to treat,so it is recommendedto consult a doctor before use.
Storage:
Store in a cool and dry place, avoid direct sunlight.Keep this product out of the reach ofchildren.
Important tips:
Before usingthis product, please read the productinstructions carefully and follow the advice of yourdoctor or professional.

STOP USE

if symptoms ofredness or allergy occur, discontinueuse and consult a physician.

KEEP OUT OF REACH OF CHILDREN SECTION

DOSAGE AND ADMINISTRATION

Use 2-3 times a day,increasing or decreasing thefrequency depending on the condition of the scar.Individualresults will be different, and the resultswill take time to verify.

STORAGE AND HANDLING

Store in a dark and cool place

INACTIVE INGREDIENT

WATER
Glycerin
Allantoin
Retinol
Panthenol
Vitamin C
Vitamin E
DIMETHICONE
Carbomer
Laurocapram
Propylene Glycol
Caprylic/capric triglyceride
Stearic Acid
Isopropyl myristate
SODIUM CARBOXYMETHYL .BETA.-GLUCAN
Centella Asiatica Extract